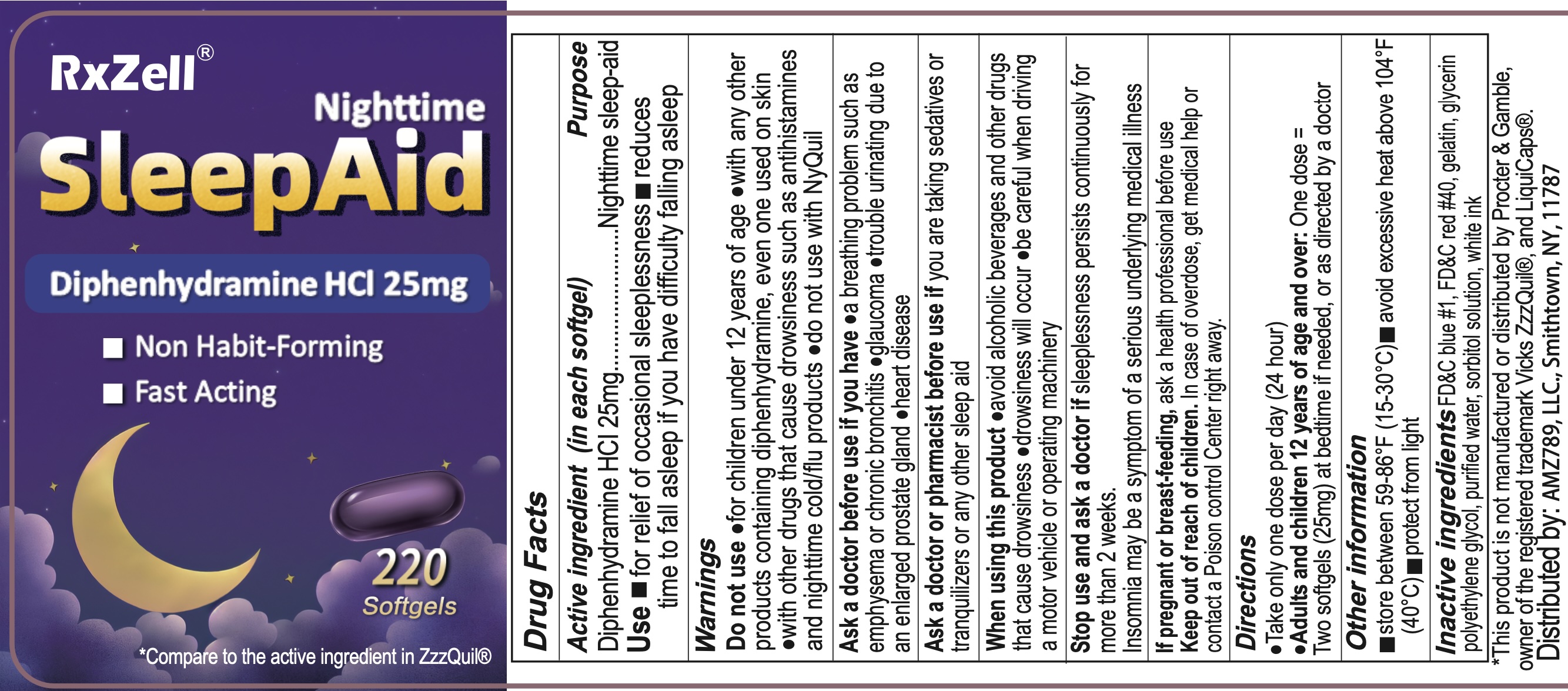 DRUG LABEL: DIPHENHYDRAMINE HYDROCHLORIDE
NDC: 73629-007 | Form: CAPSULE, LIQUID FILLED
Manufacturer: AMZ789 LLC
Category: otc | Type: HUMAN OTC DRUG LABEL
Date: 20260107

ACTIVE INGREDIENTS: DIPHENHYDRAMINE HYDROCHLORIDE 25 mg/1 1
INACTIVE INGREDIENTS: POLYETHYLENE GLYCOL, UNSPECIFIED; FD&C RED NO. 40; GLYCERIN; WATER; GELATIN; SORBITOL; FD&C BLUE NO. 1

Diphenhydramine HCl 25mg

ACTIVE INGREDIENT

Diphenhydramine HCl 25 mg

DOSAGE AND ADMINISTRATION

Diphenhydramine HCl 25 mg

PURPOSE

Nighttime sleep-aid

INDICATIONS AND USAGE

for the relief of occasional sleeplessness
reduces time to fall asleep if you have difficulty falling asleep

Warnings

DO NOT USE

- for children under 12 years of age
- with any other product containing diphenhydramine, even one used on skin
- with other drugs that cause drowsiness such as antihistamines and nighttime cold/flu products
- do not use with NyQuil

ASK DOCTOR/PHARMACIST

- a breathing problem such as asthma, emphysema, or chronic bronchitis
- glaucoma
- difficulty in urination due to enlargement of the prostate gland
- heart disease

Ask a doctor or pharmacist before use if you are taking sedatives or tranquilizers or any other sleep aid

WHEN USING

- avoid alcoholic beverages and other drugs that cause drowsiness
- drowsiness will occur
- be careful when driving a motor vehicle or operating machinery

Stop use and ask a doctor if sleeplessness persists continuously for more than 2 weeks. Insomnia may be a symptom of serious underlying medical illness.

PREGNANCY OR BREAST FEEDING

If pregnant or breast-feeding, ask a health professional before use.

Keep out of reach of children. Overdose warning: Taking more than directed can cause serious health problems. In case of overdose, get medical help or contact a Poison Control Center right away.

DOSAGE FORMS AND STRENGTHS

take only one dose per day (24 hours) - see Overdose warning

adults & Children 12 yrs & over | One dose = TWO 25mg softgels (50mg); at bedtime if needed or as directed by a doctor

INACTIVE INGREDIENT

FD&C blue #1, FD&C red #40, gelatin, glycerin, polyethylene glycol, purified water, sorbitol special and white edible ink